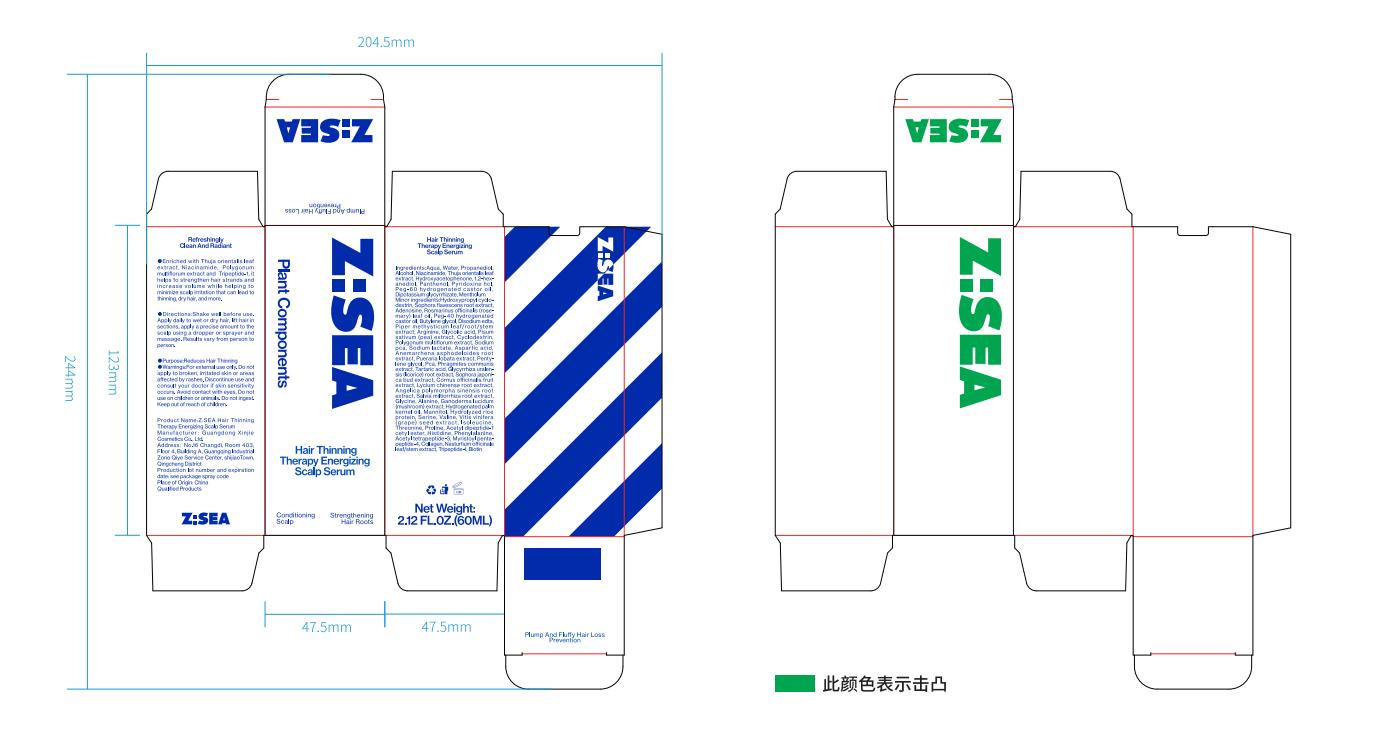 DRUG LABEL: Hair Thinning Therapy Energizing Scalp Serum
NDC: 85769-456 | Form: LOTION/SHAMPOO
Manufacturer: Guangdong Xinjie Cosmetics Co.,Ltd.
Category: homeopathic | Type: HUMAN OTC DRUG LABEL
Date: 20250605

ACTIVE INGREDIENTS: PROPANEDIOL 15 mg/1 mL
INACTIVE INGREDIENTS: SODIUM LACTATE; ALCOHOL; ACETYL DIPEPTIDE-1 CETYL ESTER; 1,2-HEXANEDIOL; WATER; PEG-40 HYDROGENATED CASTOR OIL; THREONINE; GLYCINE; SODIUM PCA; BOVINE TYPE I COLLAGEN; DIPOTASSIUM GLYCYRRHIZATE; ALANINE; PROLINE; DISODIUM EDTA-COPPER; PANTHENOL; SERINE; VALINE; ISOLEUCINE; PHENYLALANINE; BIOTIN; MANNITOL; ADENOSINE; HISTIDINE; GLYCOLIC ACID; ARGININE; CYCLODEXTRIN; ACETYL TETRAPEPTIDE-3; PEG-60 HYDROGENATED CASTOR OIL; PYRIDOXINE HCL; ROSMARINUS OFFICINALIS (ROSEMARY) LEAF OIL; HYDROLYZED RICE PROTEIN (ENZYMATIC; 2000 MW); MYRISTOYL PENTAPEPTIDE-4; TRIPEPTIDE-1; BUTYLENE GLYCOL; NIACINAMIDE; 2-BROMO-4'-HYDROXYACETOPHENONE; ASPARTIC ACID; PCA

ACTIVE INGREDIENT

WATER,PROPANEDIOL

PURPOSE

Reduces Hair

DOSAGE AND ADMINISTRATION

Net Weight:2.12 FL.OZ.(60ML)

WARNINGS

For external use only

KEEP OUT OF REACH OF CHILDREN SECTION

INACTIVE INGREDIENT

ALCOHOL,AQUA,PEG-40 HYDROGENATED CASTOR OIL,DISODIUM EDTA,NIACINAMIDE,PANTHENOL,HYDROXYACETOPHENONE,PYRIDOXINE HCL,PEG-60 HYDROGENATED CASTOR OIL,HYDROXYPROPYL CYCLODEXTRIN,DIPOTASSIUM GLYCYRRHIZATE,MENTHOLUM,ADENOSINE,SODIUM PCA,SODIUM LACTATE,ARGININE,ASPARTIC ACID,PCA,GLYCINE,ALANINE,SERINE,VALINE,ISOLEUCINE,THREONINE,PROLINE,HISTIDINE,BIOTIN,TRIPEPTIDE-1,MYRISTOYL PENTAPEPTIDE-4

INDICATIONS AND USAGE

Shake well before use.Apply dailt to wet or dry hair.lift hair in sections